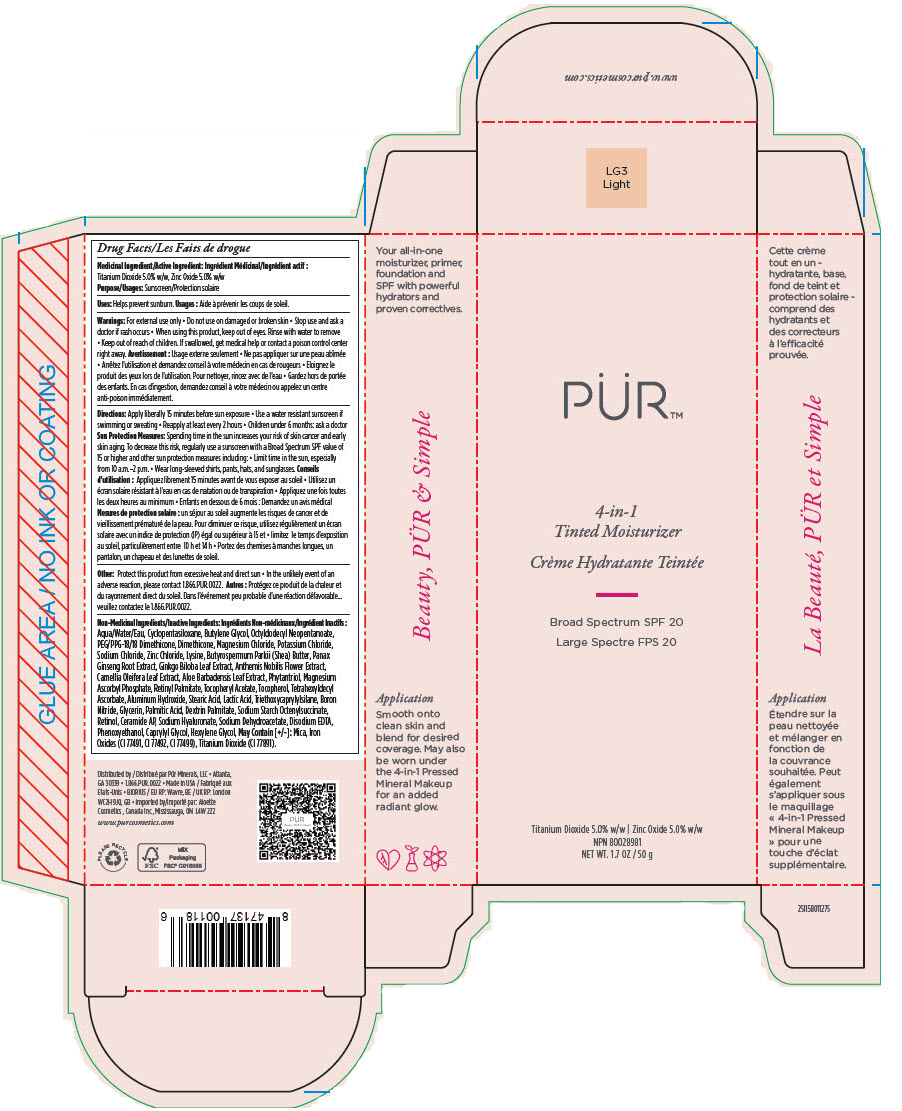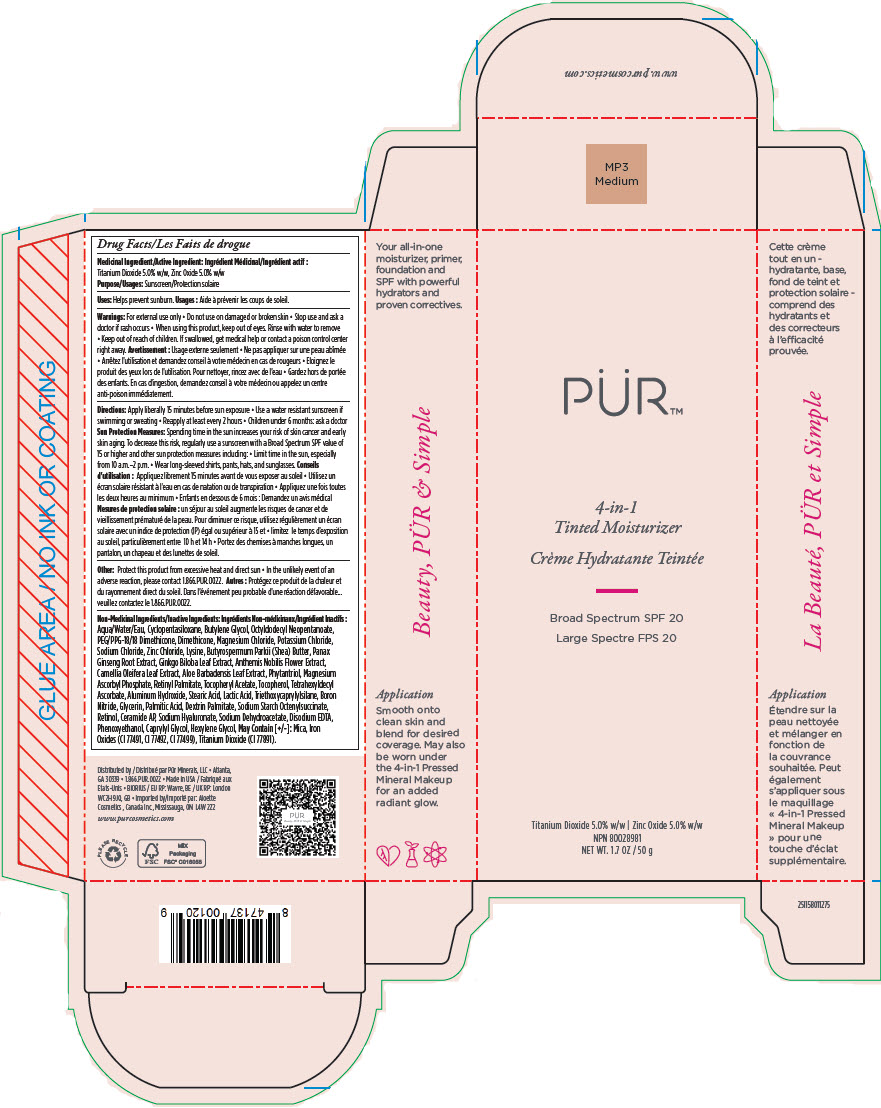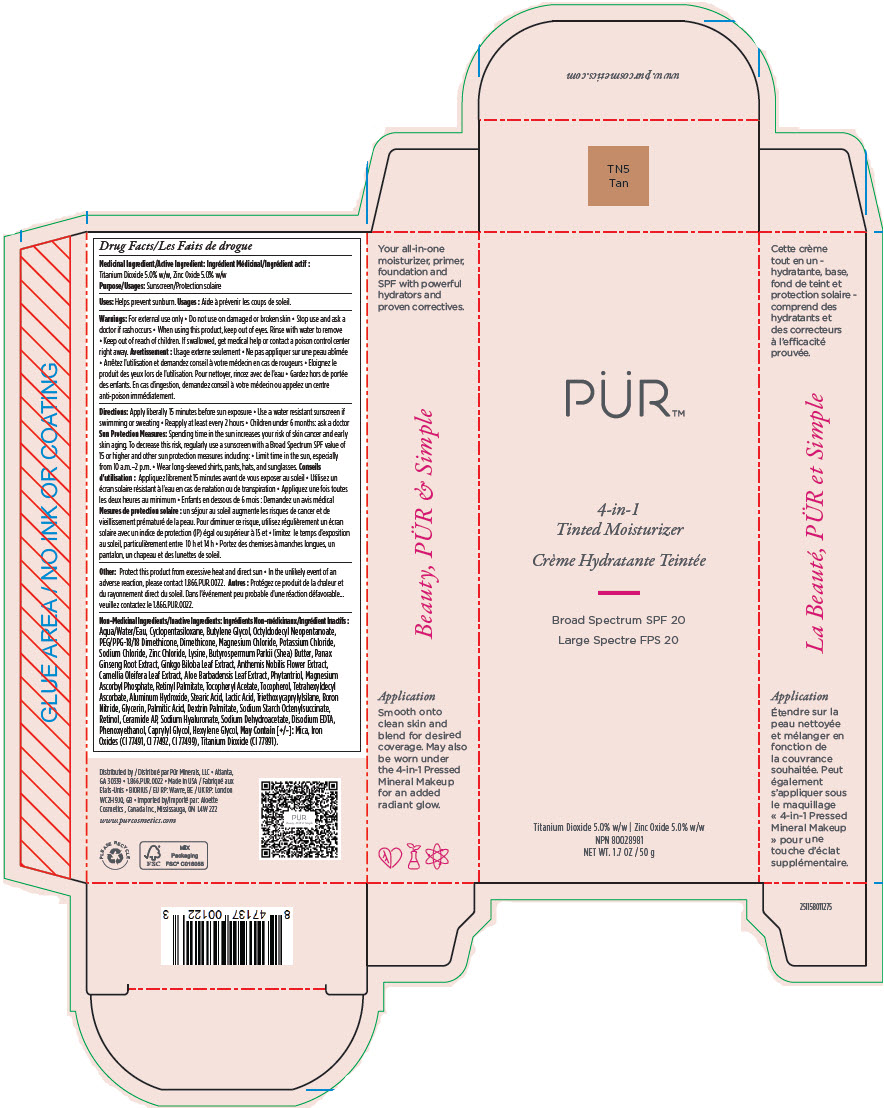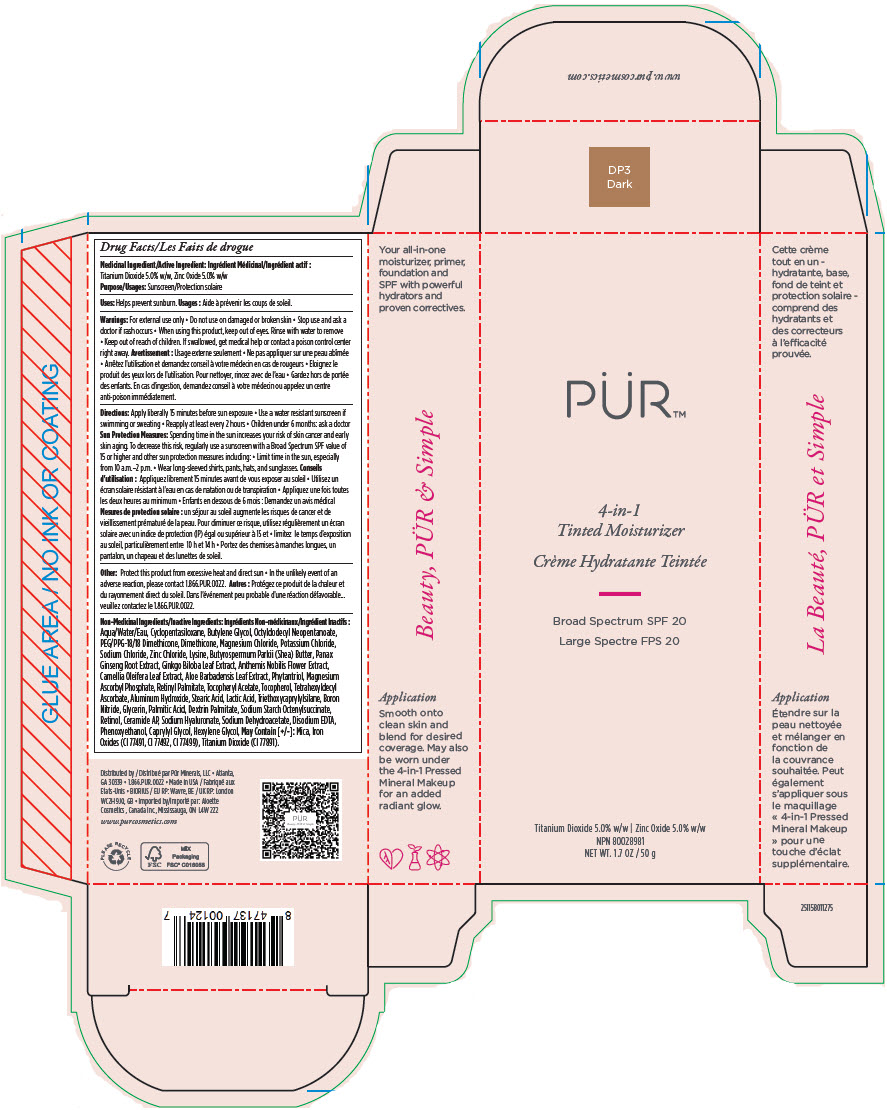 DRUG LABEL: Purminerals 4-in-1 Mineral Tinted Moisturizer Broad Spectrum SPF 20 (LIGHT)
NDC: 67345-0001 | Form: CREAM
Manufacturer: Purminerals
Category: otc | Type: HUMAN OTC DRUG LABEL
Date: 20230124

ACTIVE INGREDIENTS: Titanium Dioxide 5 g/100 g; Zinc Oxide 5 g/100 g
INACTIVE INGREDIENTS: ALOE VERA LEAF; ALUMINUM HYDROXIDE; WATER; BORON NITRIDE; BUTYLENE GLYCOL; SHEA BUTTER; CAMELLIA OLEIFERA LEAF; CAPRYLYL GLYCOL; CYCLOMETHICONE 5; DIMETHICONE; EDETATE DISODIUM; GINKGO; GLYCERIN; HEXYLENE GLYCOL; LACTIC ACID, UNSPECIFIED FORM; LYSINE; MAGNESIUM ASCORBYL PHOSPHATE; MAGNESIUM CHLORIDE; OCTYLDODECYL NEOPENTANOATE; PALMITIC ACID; ASIAN GINSENG; PEG/PPG-18/18 DIMETHICONE; PHENOXYETHANOL; PHYTANTRIOL; POTASSIUM CHLORIDE; RETINOL; VITAMIN A PALMITATE; SODIUM CHLORIDE; SODIUM DEHYDROACETATE; HYALURONATE SODIUM; STEARIC ACID; TETRAHEXYLDECYL ASCORBATE; TOCOPHEROL; .ALPHA.-TOCOPHEROL ACETATE; TRIETHOXYCAPRYLYLSILANE; ZINC CHLORIDE; FERRIC OXIDE RED; MICA

Purminerals 4-in-1 Mineral Tinted Moisturizer Broad Spectrum SPF 20

Drug Facts

Medicinal Ingredient/Active Ingredient

Titanium Dioxide 5.0% w/w, Zinc Oxide 5.0% w/w

Purpose

Sunscreen

Uses

Helps prevent sunburn.

Warnings

For external use only

- Do not use on damaged or broken skin

- Stop use and ask a doctor if rash occurs

- When using this product, keep out of eyes. Rinse with water to remove

- Keep out of reach of children. If swallowed, get medical help or contact a poison control center right away.

Directions

Apply liberally 15 minutes before sun exposure

- Use a water resistant sunscreen if swimming or sweating
- Reapply at least every 2 hours
- Children under 6 months: ask a doctor

Sun Protection Measures

Spending time in the sun increases your risk of skin cancer and early skin aging. To decrease this risk, regularly use a sunscreen with a Broad Spectrum SPF value of 15 or higher and other sun protection measures including:

- Limit time in the sun, especially from 10 a.m.–2 p.m.
- Wear long-sleeved shirts, pants, hats, and sunglasses.

Other

Protect this product from excessive heat and direct sun

- In the unlikely event of an adverse reaction, please contact 1.866.PUR.0022.

Non-Medicinal Ingredients/ Inactive Ingredients

Aqua, Cyclopentasiloxane, Butylene Glycol, Octyldodecyl Neopentanoate, PEG/PPG-18/18 Dimethicone, Dimethicone, Magnesium Chloride, Potassium Chloride, Sodium Chloride, Zinc Chloride, Lysine, Butyrospermum Parkii (Shea) Butter, Panax Ginseng Root Extract, Ginkgo Biloba Leaf Extract, Anthemis Nobilis Flower Extract, Camellia Oleifera Leaf Extract, Aloe Barbadensis Leaf Extract, Phytantriol, Magnesium Ascorbyl Phosphate, Retinyl Palmitate, Tocopheryl Acetate, Tocopherol, Tetrahexyldecyl Ascorbate, Aluminum Hydroxide, Stearic Acid, Lactic Acid, Triethoxycaprylylsilane, Boron Nitride, Glycerin, Palmitic Acid, Dextrin Palmitate, Sodium Starch Octenylsuccinate, Retinol, Ceramide AP, Sodium Hyaluronate, Sodium Dehydroacetate, Disodium EDTA, Phenoxyethanol, Caprylyl Glycol, Hexylene Glycol, May Contain: Mica, Iron Oxides (CI 77491, CI 77492, CI 77499), Titanium Dioxide (CI 77891)

Distributed by pürminerals® Atlanta, GA 30327

PRINCIPAL DISPLAY PANEL - 50 g Tube Carton - Light

PÜR™

4-in-1
Tinted Moisturizer

Broad Spectrum SPF 20

Titanium Dioxide 5.0% w/w | Zinc Oxide 5.0% w/w
NPN 80028981
NET WT. 1 .7 OZ / 50 g

PRINCIPAL DISPLAY PANEL - 50 g Tube Carton - Medium

PÜR™

4-in-1
Tinted Moisturizer

Broad Spectrum SPF 20

Titanium Dioxide 5.0% w/w | Zinc Oxide 5.0% w/w
NPN 80028981
NET WT. 1 .7 OZ / 50 g

PRINCIPAL DISPLAY PANEL - 50 g Tube Carton - Tan

PÜR™

4-in-1
Tinted Moisturizer

Broad Spectrum SPF 20

Titanium Dioxide 5.0% w/w | Zinc Oxide 5.0% w/w
NPN 80028981
NET WT. 1 .7 OZ / 50 g

PRINCIPAL DISPLAY PANEL - 50 g Tube Carton - Dark

PÜR™

4-in-1
Tinted Moisturizer

Broad Spectrum SPF 20

Titanium Dioxide 5.0% w/w | Zinc Oxide 5.0% w/w
NPN 80028981
NET WT. 1 .7 OZ / 50 g